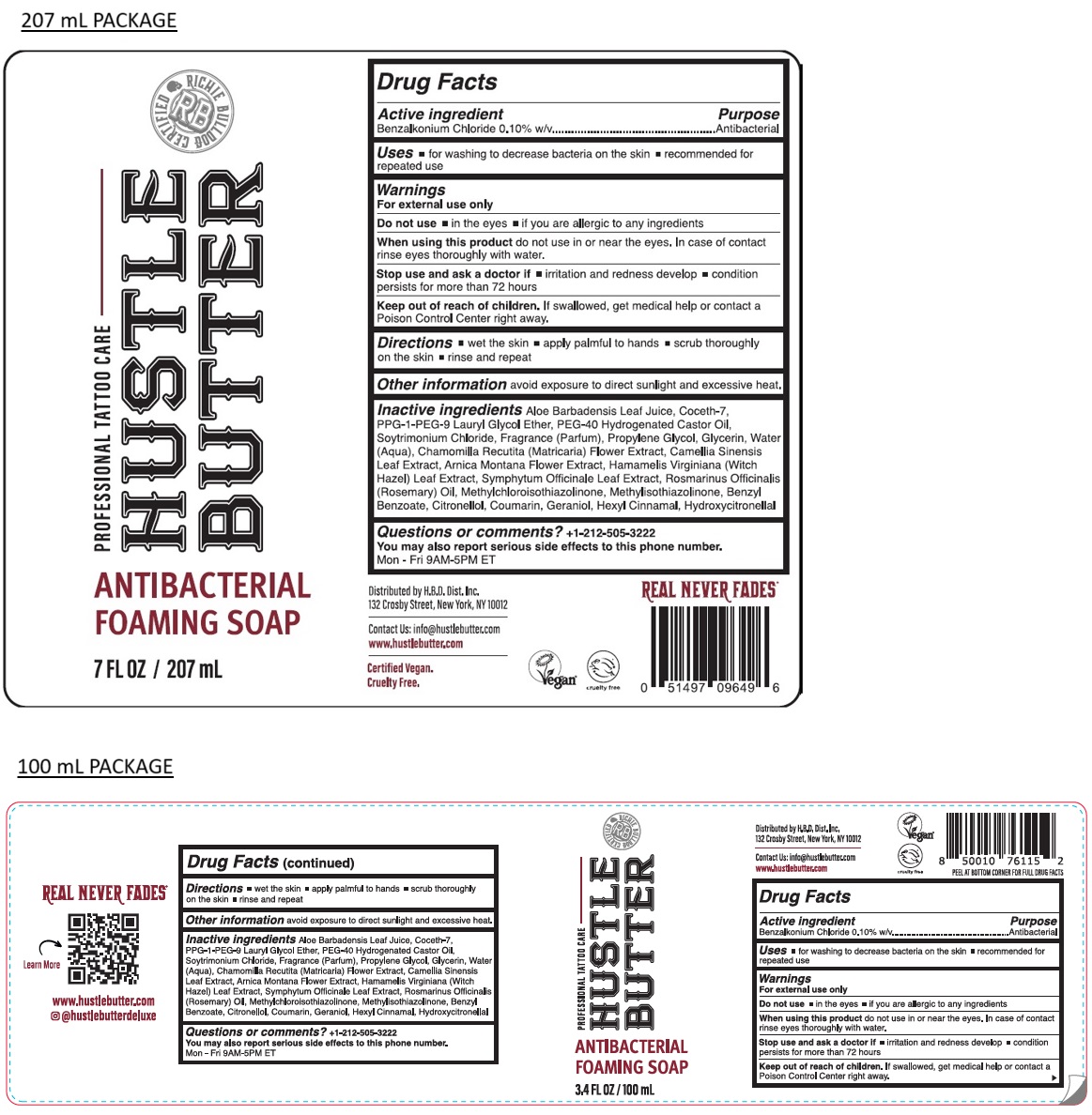 DRUG LABEL: HUSTLE BUTTER ANTIBACTERIAL FOAMING
NDC: 72014-200 | Form: SOAP
Manufacturer: H.B.D. DIST. INC.
Category: otc | Type: HUMAN OTC DRUG LABEL
Date: 20260109

ACTIVE INGREDIENTS: BENZALKONIUM CHLORIDE 0.1 g/100 mL
INACTIVE INGREDIENTS: ALOE VERA LEAF; COCETH-7; PPG-1-PEG-9 LAURYL GLYCOL ETHER; POLYOXYL 40 HYDROGENATED CASTOR OIL; TRIMETHYLAMINE HYDROCHLORIDE; PROPYLENE GLYCOL; GLYCERIN; WATER; CHAMOMILE; GREEN TEA LEAF; ARNICA MONTANA FLOWER; HAMAMELIS VIRGINIANA LEAF; COMFREY LEAF; ROSEMARY OIL; METHYLCHLOROISOTHIAZOLINONE; METHYLISOTHIAZOLINONE; BENZYL BENZOATE; .BETA.-CITRONELLOL, (R)-; COUMARIN; GERANIOL; .ALPHA.-HEXYLCINNAMALDEHYDE; HYDROXYCITRONELLAL

HUSTLE BUTTER ANTIBACTERIAL FOAMING SOAP

Active ingredient

Benzalkonium Chloride 0.10% w/v

Purpose

Antibacterial

Uses

• for washing to decrease bacteria on the skin • recommended for repeated use

Warnings

For external use only

Do not use • in the eyes • if you are allergic to any ingredients

When using this product do not use in or near the eyes. In case of contact rinse eyes thoroughly with water.

Stop use and ask a doctor if • irritation and redness develop • condition persists for more than 72 hours

Keep out of reach of children. If swallowed, get medical help or contact a Poison Control Center right away.

Directions

• wet the skin • apply palmful to hands • scrub thoroughly on the skin • rinse and repeat

Other information

avoid exposure to direct sunlight and excessive heat.

Inactive ingredients

Aloe Barbadensis Leaf Juice, Coceth-7, PPG-1-PEG-9 Lauryl Glycol Ether, PEG-40 Hydrogenated Castor Oil, Soytrimonium Chloride, Fragrance (Parfum), Propylene Glycol, Glycerin, Water (Aqua), Chamomilla Recutita (Matricaria) Flower Extract, Camellia Sinensis Leaf Extract, Arnica Montana Flower Extract, Hamamelis Virginiana (Witch Hazel) Leaf Extract, Symphytum Officinale Leaf Extract, Rosmarinus Officinalis (Rosemary) Oil, Methylchloroisothiazolinone, Methylisothiazolinone, Benzyl Benzoate, Citronellol, Coumarin, Geraniol, Hexyl Cinnamal, Hydroxycitronellal

Questions or comments?

+1-212-505-3222
You may also report serious side effects to this phone number.
Mon - Fri 9AM-5PM ET

PROFESSIONAL TATTOO CARE

Distributed by H.B.D. Dist. Inc.
132 Crosby Street, New York, NY 10012

Contact Us: info@hustlebutter.com
www. hustlebutter.com

Certified Vegan.
Cruelty Free.

REAL NEVER FADES®